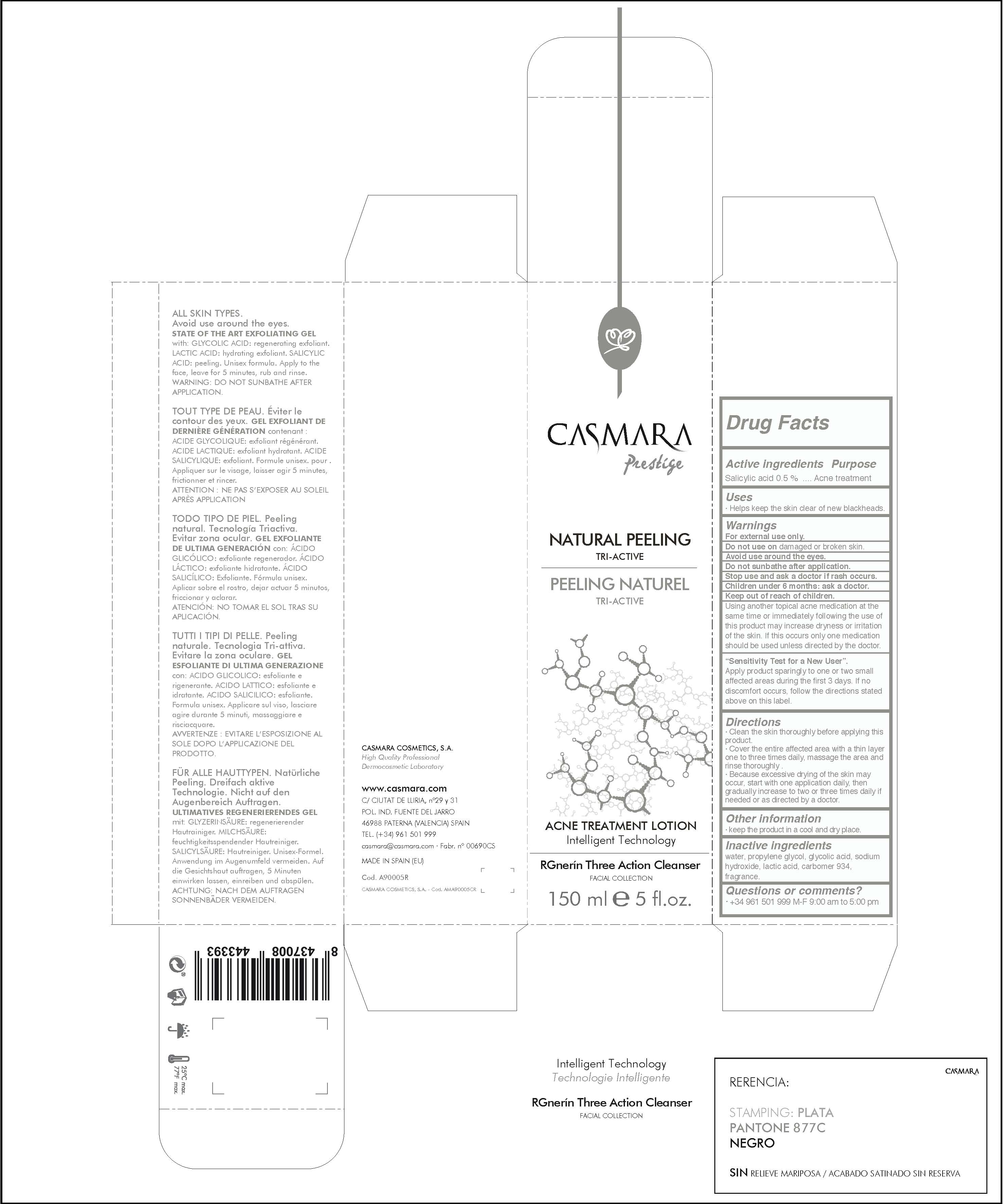 DRUG LABEL: Natural Peeling TriActive Acne
NDC: 20151-076 | Form: LOTION
Manufacturer: Casmara Cosmetics, SA
Category: otc | Type: HUMAN OTC DRUG LABEL
Date: 20161101

ACTIVE INGREDIENTS: SALICYLIC ACID 0.5 mg/1 mL
INACTIVE INGREDIENTS: WATER 48.5 mg/1 mL; PERFLUNAFENE 0.1 mg/1 mL; CARBOMER 934 1.5 mg/1 mL; PROPANEDIOL 40 mg/1 mL; GLYCOLIC ACID 5.6 mg/1 mL; SODIUM HYDROXIDE 2 mg/1 mL; LACTIC ACID 1.8 mg/1 mL

Natural Peeling Tri Active. Acne treatment lotion

Stop use and ask a doctor if rash occurs

Children under 6 months: ask a doctor

. keep out of reach of children

Questions or comments? + 34 961 501 099 M-F 9:00 am to 5:00 pm

OTHER SAFETY INFORMATION

. keep the product in a cool and dry place

Directions

. clean the skin thoroughly before applying this product

. cover the entire affected area with a thin layer one to three times daily, massage the area and rinse thoroughly.

. because excessive dryness of the skin may occur, start with one application daily, then gradually increase to two or three times daily if needed or as directed by a doctor

DOSAGE AND ADMINISTRATION

. clean the skin thoroughly before applying this product

. cover the entire affected area with a thin layer one to three times daily, massage the area and rinse thoroughly.

. because excessive dryness of the skin may occur, start with one application daily, then gradually increase to two or three times daily if needed or as directed by a doctor

Uses

. helps keep the skin clear of new blakcheads

PURPOSE

. acne treatment lotion

. helps the skin clear of new blackheads

Active Ingredients

Salicylic acid 0.5%........................... Acne Treatment

INACTIVE INGREDIENT

water, propylene glycol, glycolic acid, sodium hydroxide, lactic acid, carbomer 934, fragrance.

WARNINGS

For external use only.

Do not use on damaged or broken skin.

Avoid use around the eyes

Do not sunbathe after application

Stop use and ask a doctor if rash occurs.

Children under 6 months: as a doctor.

KEEP OUT OF THE REACH OF CHILDREN

USING OTHER TOPICAL ACNE DRUGS AT THE SAME TIME OR INMEDIATELY FOLLOWING THE USE OF THIS PRODUCT MAY INCREASE DRYNESS OR IRRITATION OF THE SKIN. IF THIS OCCURS, ONLY ONE MEDICATION SHOULD BE USED UNLESS DIRECTED BY A DOCTOR

Sensitive Test for a New User

Apply product sparingly to one or two small affected areas during the first three days. If not discomfort occurs follow the directions state above in this label.

PACKAGE LABEL

Natural Peeling Tri Active

Acne Treatment Lotion

Intelligent Technology

Rgnerin Three Action Cleaner

Facial Collection